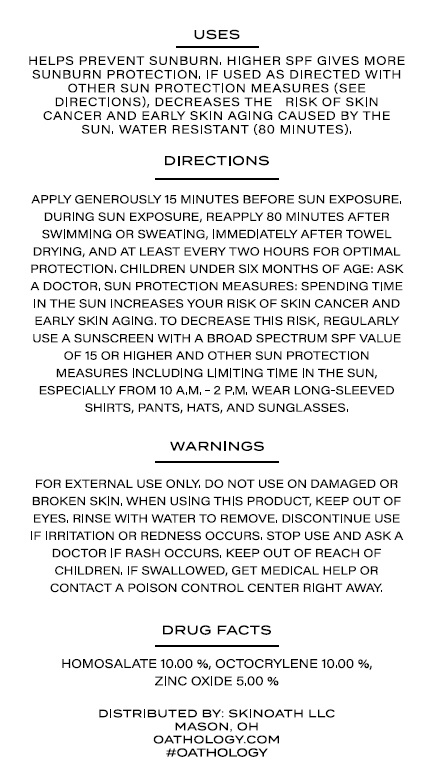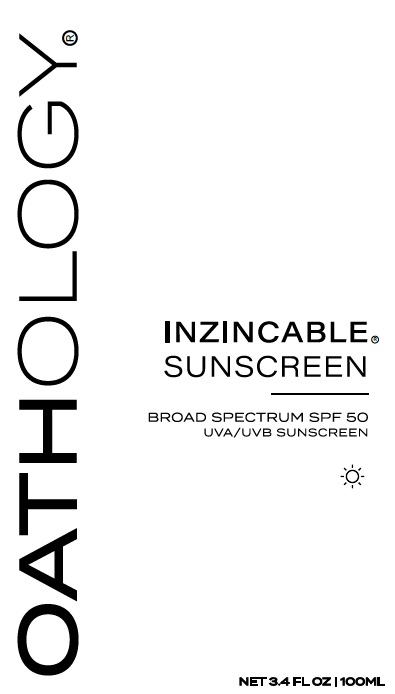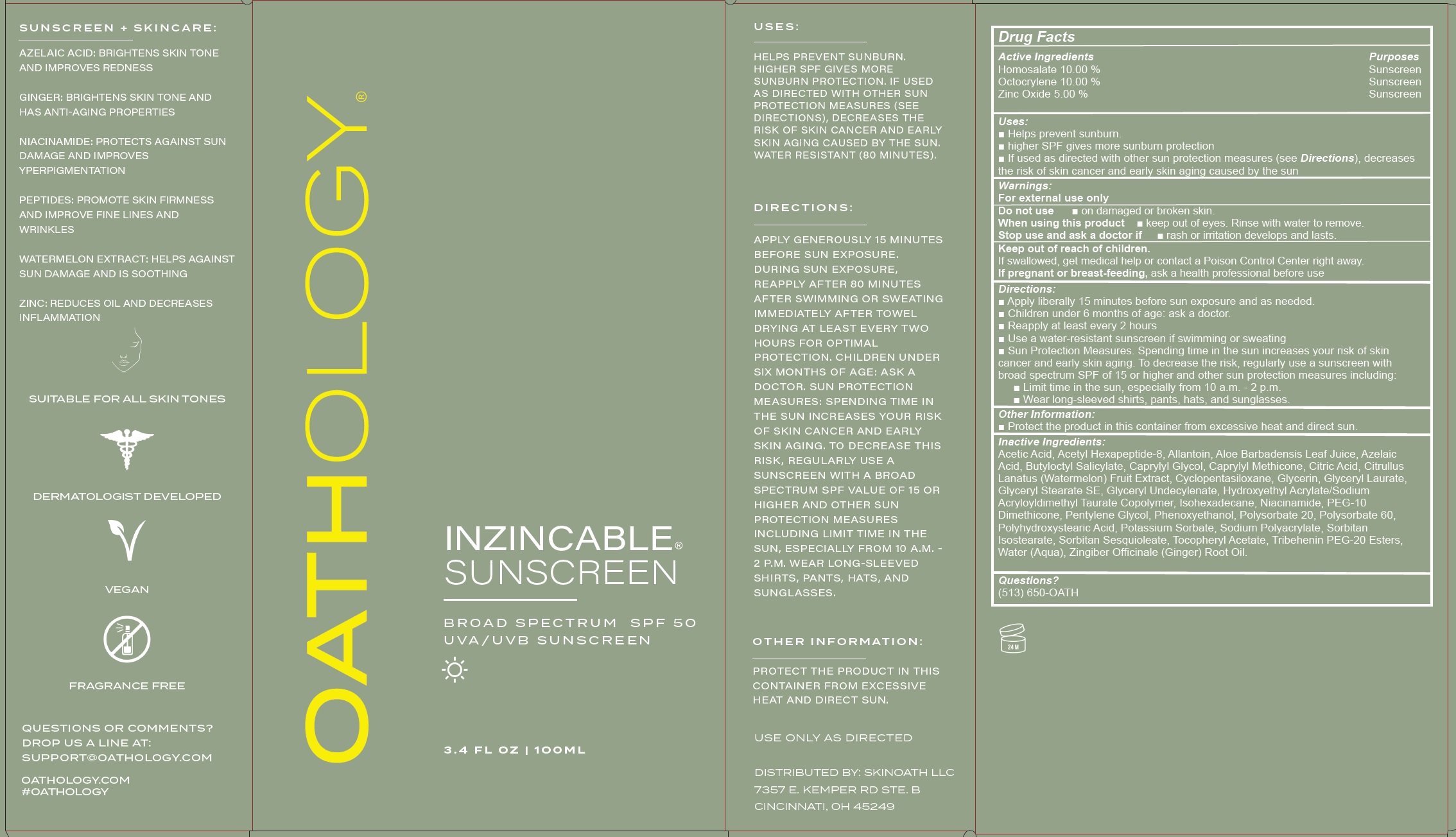 DRUG LABEL: Oathology Inzincable Sunscreen SPF 50
NDC: 85562-594 | Form: LOTION
Manufacturer: SKINOATH LLC
Category: otc | Type: HUMAN OTC DRUG LABEL
Date: 20250422

ACTIVE INGREDIENTS: HOMOSALATE 100 mg/1 mL; OCTOCRYLENE 100 mg/1 mL; ZINC OXIDE 50 mg/1 mL
INACTIVE INGREDIENTS: ACETIC ACID; ACETYL HEXAPEPTIDE-8 AMIDE; ALLANTOIN; ALOE VERA LEAF; AZELAIC ACID; BUTYLOCTYL SALICYLATE; CAPRYLYL GLYCOL; CAPRYLYL TRISILOXANE; CITRIC ACID MONOHYDRATE; WATERMELON; CYCLOMETHICONE 5; GLYCERIN; GLYCERYL LAURATE; GLYCERYL STEARATE SE; ISOHEXADECANE; NIACINAMIDE; PENTYLENE GLYCOL; PHENOXYETHANOL; POLYSORBATE 20; POLYSORBATE 60; POTASSIUM SORBATE; SORBITAN ISOSTEARATE; SORBITAN SESQUIOLEATE; .ALPHA.-TOCOPHEROL ACETATE; TRIBEHENIN PEG-20 ESTERS; WATER; GINGER OIL

Oathology Inzincable Sunscreen SPF 50

Active Ingredients

Homosalate 10.00 %
Octocrylene 10.00 %
Zinc Oxide 5.00 %

Purposes

Sunscreen

Uses:

- Helps prevent sunburn.
- higher SPF gives more sunburn protection
- If used as directed with other sun protection measures (see Directions), decreases the risk of skin cancer and early skin aging caused by the sun

Warnings:

For external use only

Do not use

- on damaged or broken skin.

When using this product

- keep out of eyes. Rinse with water to remove.

Stop use and ask a doctor if

- rash or irritation develops and lasts.

Keep out of reach of children.

If swallowed, get medical help or contact a Poison Control Center right away.

If pregnant or breast-feeding,

ask a health professional before use

Directions:

- Apply liberally 15 minutes before sun exposure and as needed.
- Children under 6 months of age: ask a doctor.
- Reapply at least every 2 hours
- Use a water-resistant sunscreen if swimming or sweating
- Sun Protection Measures.Spending time in the sun increases your risk of skin cancer and early skin aging. To decrease the risk, regularly use a sunscreen with broad spectrum SPF of 15 or higher and other sun protection measures including:
- Limit time in the sun, especially from 10 a.m. - 2 p.m.
- Wear long-sleeved shirts, pants, hats, and sunglasses.

Other Information:

- Protect the product in this container from excessive heat and direct sun.

Inactive Ingredients:

Acetic Acid, Acetyl Hexapeptide-8, Allantoin, Aloe Barbadensis Leaf Juice, Azelaic Acid, Butyloctyl Salicylate, Caprylyl Glycol, Caprylyl Methicone, Citric Acid, Citrullus Lanatus (Watermelon) Fruit Extract, Cyclopentasiloxane, Glycerin, Glyceryl Laurate, Glyceryl Stearate SE, Glyceryl Undecylenate, Hydroxyethyl Acrylate/Sodium Acryloyldimethyl Taurate Copolymer, Isohexadecane, Niacinamide, PEG-10 Dimethicone, Pentylene Glycol, Phenoxyethanol, Polysorbate 20, Polysorbate 60, Polyhydroxystearic Acid, Potassium Sorbate, Sodium Polyacrylate, Sorbitan Isostearate, Sorbitan Sesquioleate, Tocopheryl Acetate, Tribehenin PEG-20 Esters, Water (Aqua), Zingiber Officinale (Ginger) Root Oil.

Questions?

(513) 650-OATH